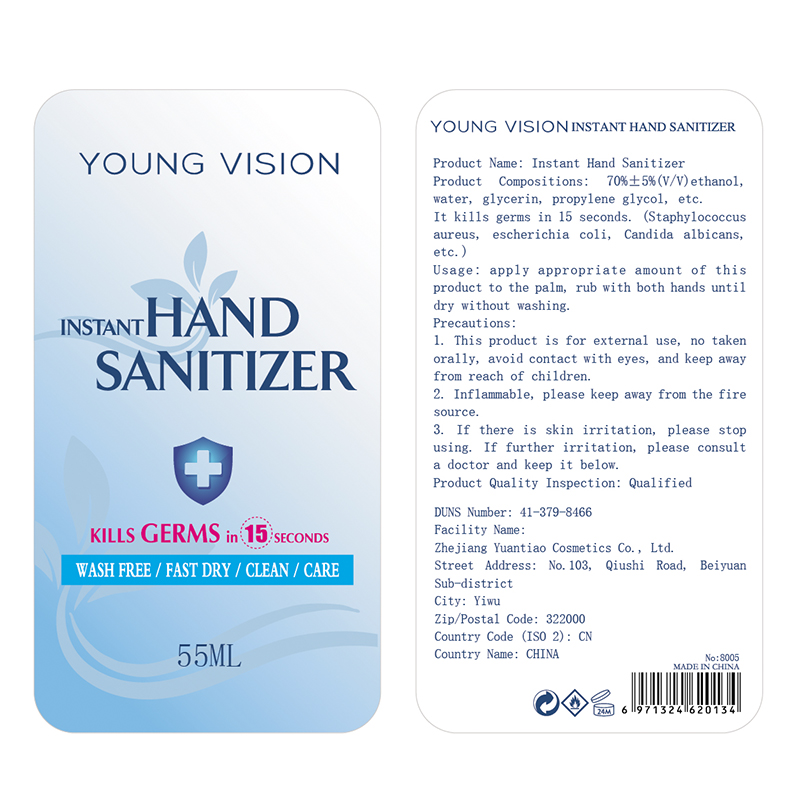 DRUG LABEL: HAND SANITIZER
NDC: 74737-2011 | Form: GEL
Manufacturer: Zhejiang Yuantiao Cosmetics Co., Ltd.
Category: otc | Type: HUMAN OTC DRUG LABEL
Date: 20200528

ACTIVE INGREDIENTS: ALCOHOL 38.5 mL/55 mL
INACTIVE INGREDIENTS: GLYCERIN 0.275 mL/55 mL; CARBOMER HOMOPOLYMER, UNSPECIFIED TYPE 0.165 mL/55 mL; WATER 15.675 mL/55 mL; PROPYLENE GLYCOL 0.275 mL/55 mL; AMINOMETHYLPROPANOL 0.11 mL/55 mL

YuanTiao, Hand Sanitizer, Gel, 70% Alcohol

Active Ingredient(s)

Alcohol 70% v/v. Purpose: Antiseptic

Purpose

Antiseptic, Hand Sanitizer

Use

Hand Sanitizer to help reduce bacteria that potentially can cause disease. For use when soap and water are not available.

Warnings

Flammable. For external use only. Keep away from heat or flame.

Do not use

- on children less than 2 months of age
- on open skin wounds

When using this product keep out of eyes, ears, and mouth.

In case of contact with eyes, rinse eyes thoroughly with water.

Stop use and ask a doctor if irritation or rash occurs. These may be signs of a serious condition.

Keep out of reach of children. If swallowed, get medical help or contact a Poison Control Center right away.

Directions

- Place enough product on hands to cover all surfaces. Rub hands together until dry.
- Supervise children under 6 years of age when using this product to avoid swallowing.

Other information

- Store between 59-86℉ (15-30℃)
- Avoid freezing and excessive heat above 104℉ (40℃)

Inactive ingredients

Water, Propylene Glycol, Glycerol, Carbomer, Aminomethyl Propanol